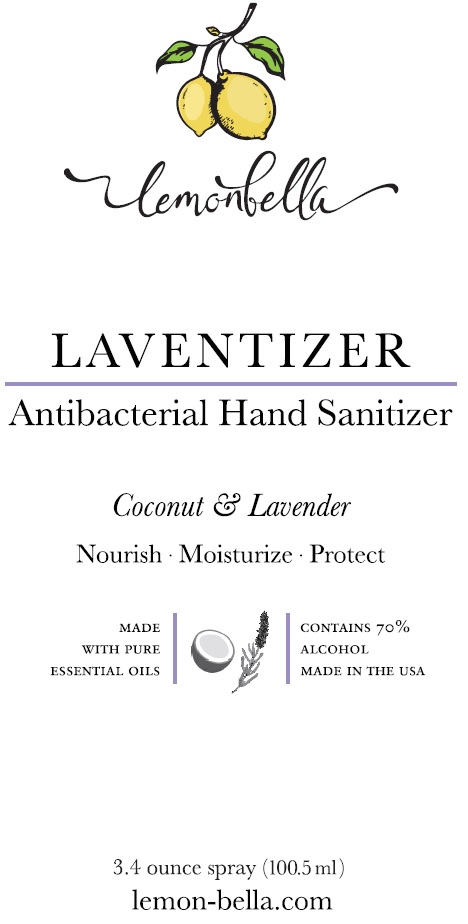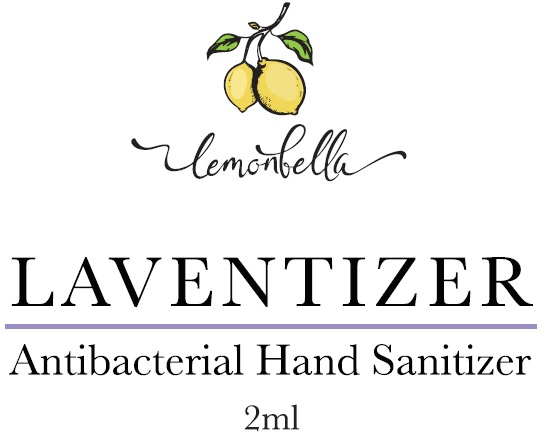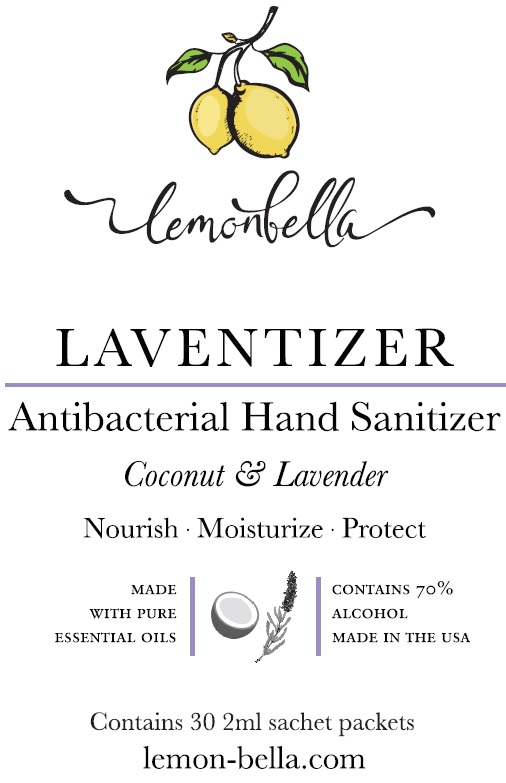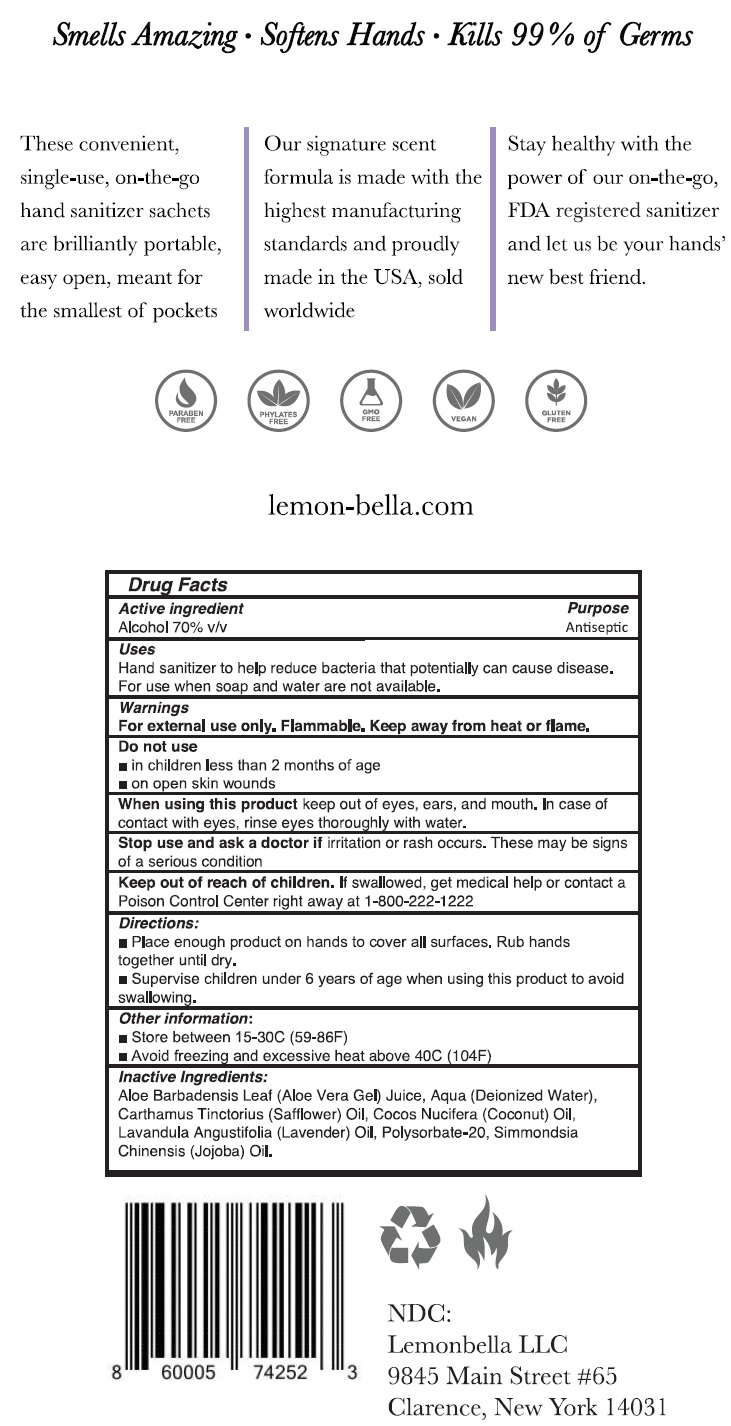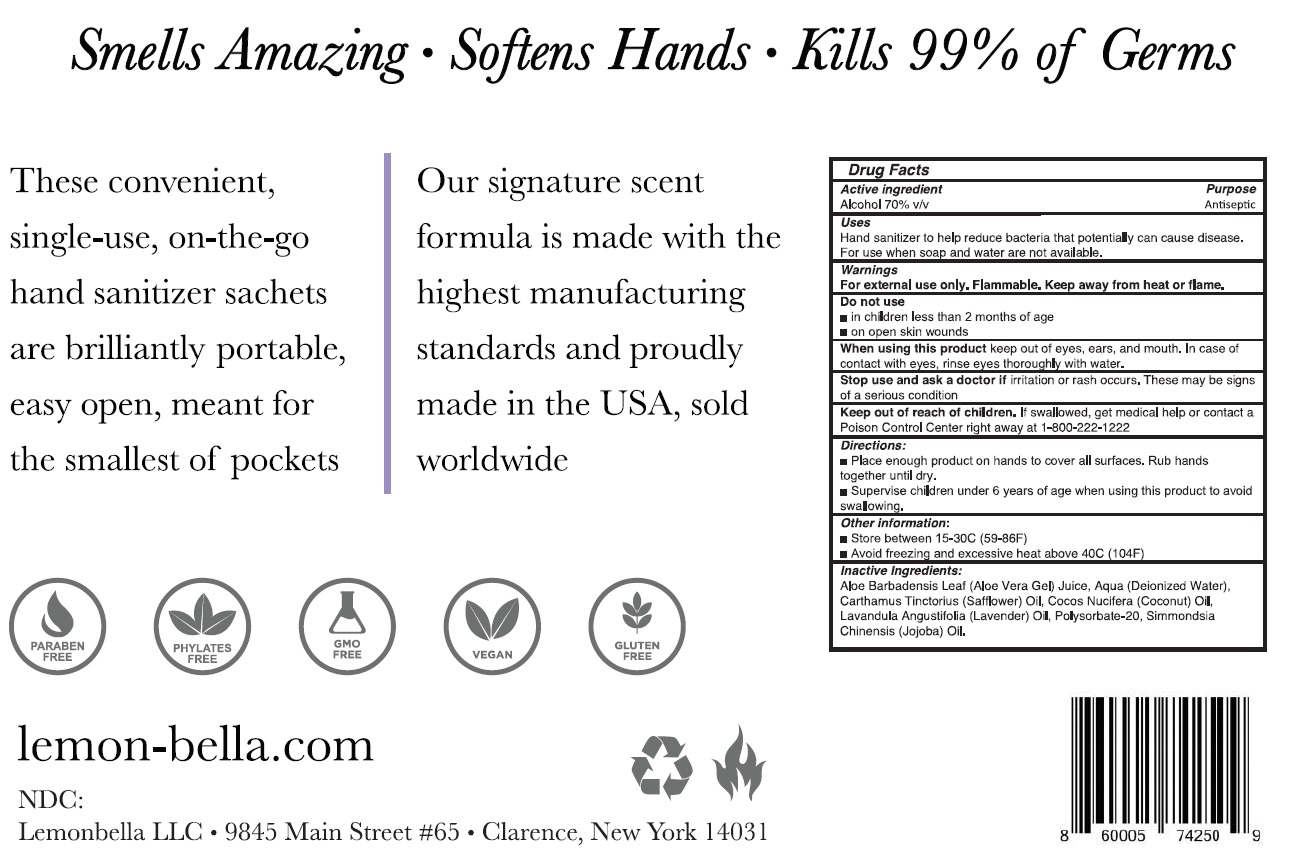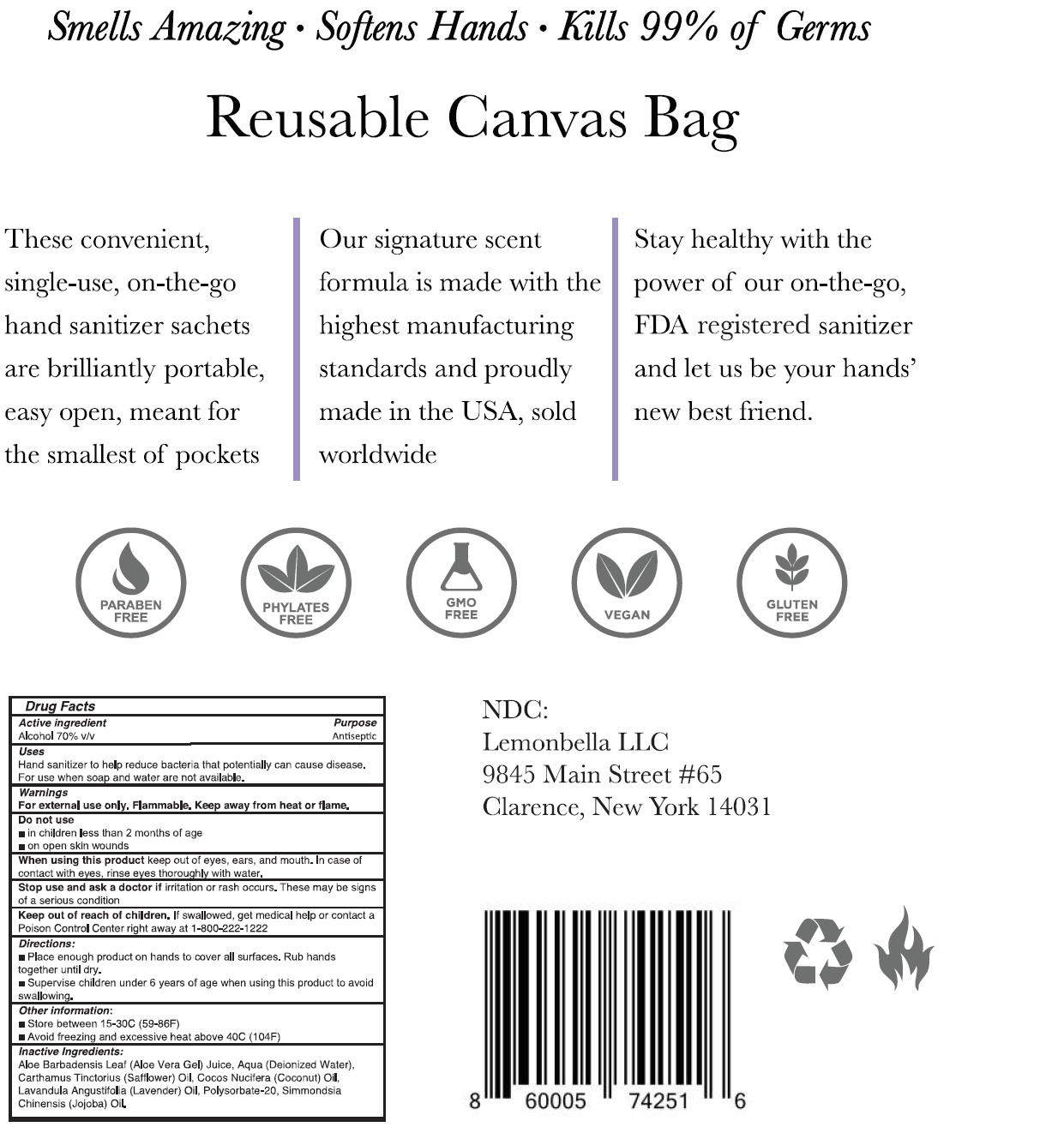 DRUG LABEL: LEMONBELLA Lavender Hand Sanitizer
NDC: 81319-112 | Form: GEL
Manufacturer: Lemonbella LLC
Category: otc | Type: HUMAN OTC DRUG LABEL
Date: 20231111

ACTIVE INGREDIENTS: ALCOHOL 0.7 mL/1 mL
INACTIVE INGREDIENTS: ALOE VERA LEAF; WATER; SAFFLOWER; COCONUT OIL; LAVENDER OIL; POLYSORBATE 20; JOJOBA OIL

LEMONBELLA Lavender Hand Sanitizer

Active ingredient

Alcohol 70% v/v

Purpose

Antiseptic

Uses

Hand sanitizer to help reduce bacteria that potentially can cause disease. For use when soap and water are not available.

Warnings

For external use only. Flammable. Keep away from heat or flame.

Do not use

- in children less than 2 months of age
- on open skin wounds

When using this product

keep out of eyes, ears, and mouth. In case of contact with eyes, rinse eyes thoroughly with water.

Stop use and ask a doctor if

irritation or rash occurs. These may be signs of a serious condition

Keep out of reach of children.

If swallowed, get medical help or contact a Poison Control Center right away at 1-800-222-1222

Directions:

- Place enough product on hands to cover all surfaces. Rub hands together until dry.
- Supervise children under 6 years of age when using this product to avoid swallowing.

Other information:

- Store between 15-30C (59-86F)
- Avoid freezing and excessive heat above 40C (104F)

Inactive Ingredients:

Aloe Barbadensis Leaf (Aloe Vera Gel) Juice, Aqua (Deionized Water), Carthamus Tinctorius (Safflower) Oil, Cocos Nucifera (Coconut) Oil, Lavandula Angustifolia (Lavender) Oil, Polysorbate-20, Simmondsia Chinensis (Jojoba) Oil.